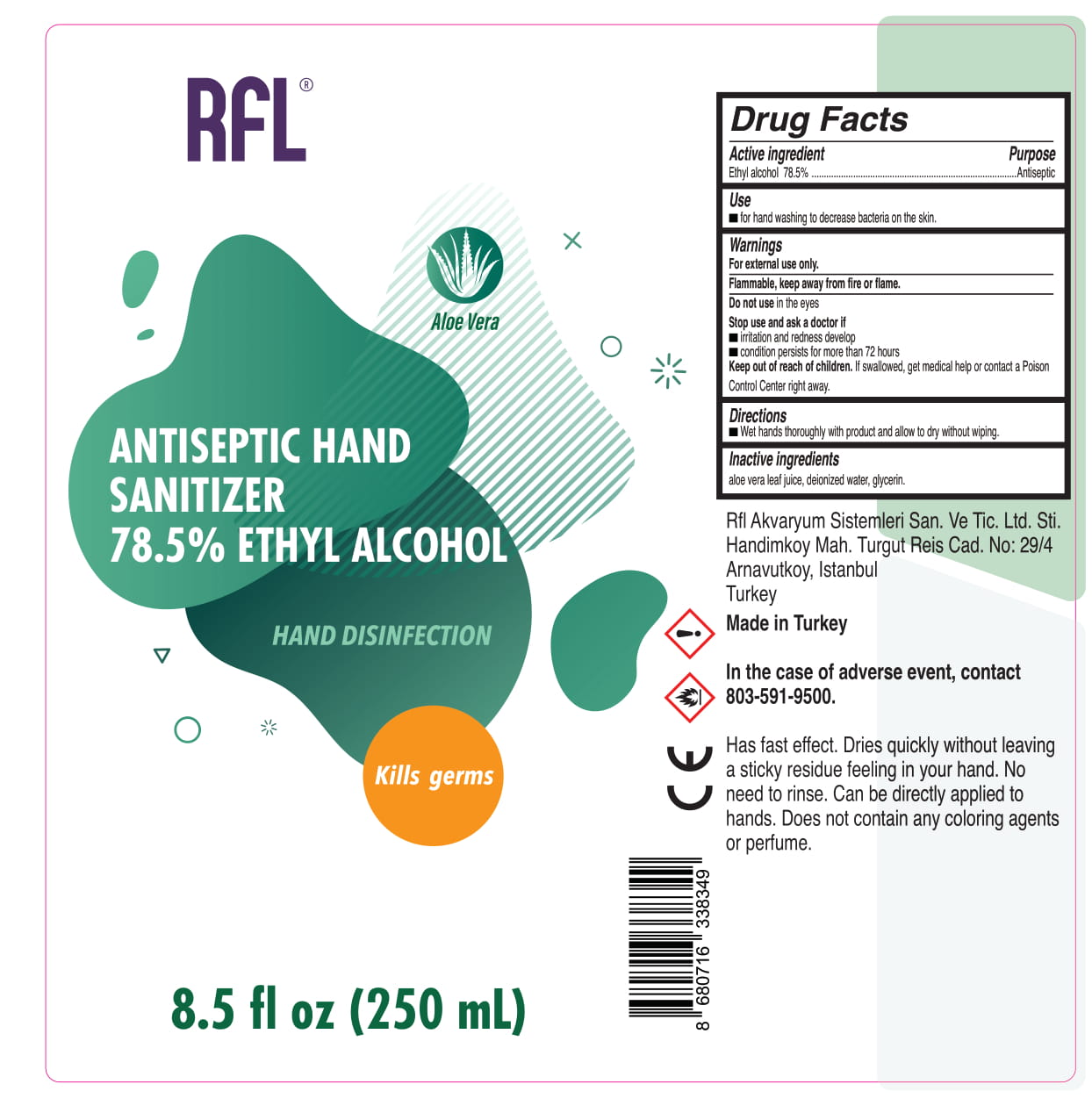 DRUG LABEL: RFL Antiseptic Hand Sanitizer
NDC: 86807-001 | Form: LIQUID
Manufacturer: RFL AKVARYUM SISTEMLERI SANAYI VE TICARET LIMITED SIRKETI
Category: otc | Type: HUMAN OTC DRUG LABEL
Date: 20220125

ACTIVE INGREDIENTS: ALCOHOL 78.5 mL/100 mL
INACTIVE INGREDIENTS: GLYCERIN; ALOE VERA LEAF; WATER

RFL ANTISEPTIC HAND SANITIZER

This is a hand sanitizer manufactured according to the Temporary Policy for Preparation of Certain Alcohol-Based Hand Sanitizer Products During the Public Health Emergency (CoViD-19); Guidance for Industry.

The hand sanitizer is manufactured using only the following United States Pharmacopoeia (USP) grade ingredients in the preparation of the product (percentage in final product formulation) consistent with World Health Organization (WHO) recommendations:

1. Alcohol (ethanol) (USP or Food Chemical Codex (FCC) grade) (78,5%, volume/volume (v/v)) in an aqueous solution denatured according to Alcohol and Tobacco Tax and Trade Bureau regulations in 27 CFR part 20.
2. Glycerol
3. Aloe vera leaf juice
4. Sterile distilled water or boiled cold water.

The firm does not add other active or inactive ingredients. Different or additional ingredients may impact the quality and potency of the product.

Active Ingredient(s)

Alcohol 78,5% v/v. Purpose: Antiseptic

Purpose

Antiseptic, Hand Sanitizer

Use

for hand washing to decrease bacteria on the skin.

Warnings

For external use only. Flammable. Keep away from fire or flame

Do not use

- in the eyes.

Stop use and ask a doctor if

-irritation and redness develop.

-condition persists for more than 72 hours.
Keep out of reach of children. If swallowed, get medical help or contact a Poison Control Center right away.

Stop use and ask a doctor if irritation or rash occurs. These may be signs of a serious condition.

Keep out of reach of children. If swallowed, get medical help or contact a Poison Control Center right away.

Directions

- Wet hands thoroughly with product and allow to dry without wiping.

Other information

- Store between 15-30C (59-86F)
- Avoid freezing and excessive heat above 40C (104F)

Inactive ingredients

aloe vera leaf juice, deionized water, glycerin.

Package Label - Principal Display Panel

250 mL NDC: 86807-001-01